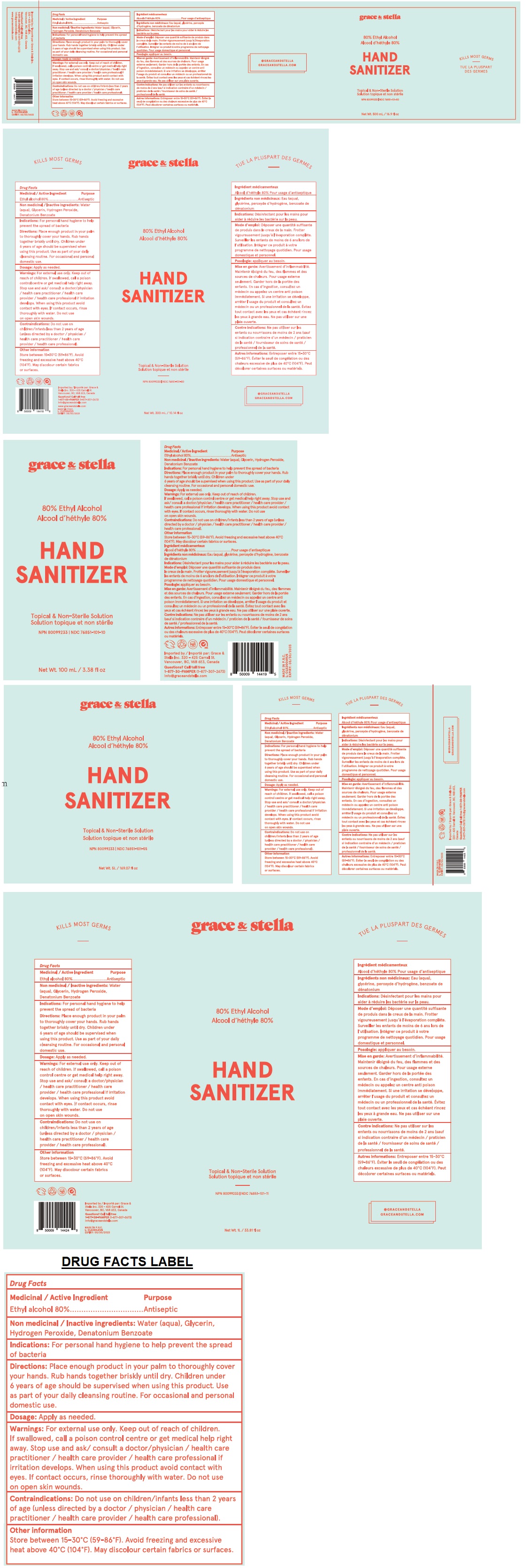 DRUG LABEL: Grace and Stella Hand Sanitizer
NDC: 76851-101 | Form: LIQUID
Manufacturer: Grace & Stella Inc
Category: otc | Type: HUMAN OTC DRUG LABEL
Date: 20200429

ACTIVE INGREDIENTS: ALCOHOL 80 mL/100 mL
INACTIVE INGREDIENTS: WATER; GLYCERIN; HYDROGEN PEROXIDE; DENATONIUM BENZOATE

grace & stella HAND SANITIZER

Medicinal / Active Ingredient

Ethyl alcohol 80%

Purpose

Antiseptic

INACTIVE INGREDIENT

Non medicinal / Inactive ingredients: Water (aqua), Glycerin, Hydrogen Peroxide, Denatonim Benzoate

INDICATIONS AND USAGE

Indications: For personal hand hygiene to help prevent the spread of bacteria

DOSAGE AND ADMINISTRATION

Directions: Place enough product in your palm to thoroughly cover your hands. Rub hands together briskly until dry. Children under 6 years of age should be supervised when using this product. Use as part of your daily cleansing routine. For occasional and personal domestic use.

Dosage: Applied as needed

Warnings: For external use only.

Stop use and ask/ consult a doctor/ physician / health care practitioner / health care provider / health care professional if irritation develops.

When using this product avoid contact with eyes. If contact occurs, rinse thoroughly with water. Do not use on open skin wounds.

Contraindications: Do not use on children/infants less than 2 years of age (unless directed by a doctor / physician / health care practitioner / health care provider / health care professional).

Keep out of reach of children. If swallowed, call a poison control centre or get medical help right away.

Other information

Store between 15-30°C (59 - 86°F). Avoid freezing and excessive heat above 40°C (104°F). May discolour certain fabrics or surfaces.

Topical & Non-Sterile Solution

@GRACEANDSTELLA

GRACEANDSTELLA.COM

KILLS MOST GERMS

Imported by: Grace & Stella Inc.

320 - 425 Carrall St.

Vancouver, BC, V6B 6E3, Canada

Questions?? Call toll free

1-877-30-PAMPER (1-877-307-2673)

info@graceandstella.com

www.graceandstella.com

MADE IN P.R.C.

EXPIRY: 05/30/2023